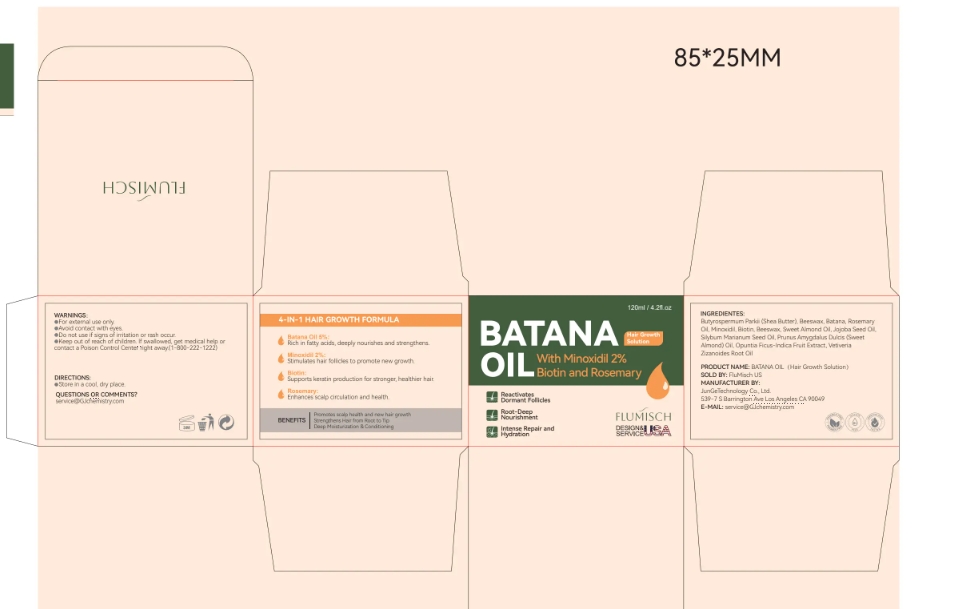 DRUG LABEL: FluMisch Batana Oil for Hair Growth
NDC: 85212-0035 | Form: OIL
Manufacturer: FluMisch Batana Oil for Hair Growth
Category: otc | Type: HUMAN OTC DRUG LABEL
Date: 20250511

ACTIVE INGREDIENTS: MINOXIDIL 2 g/100 mL
INACTIVE INGREDIENTS: OPUNTIA FICUS-INDICA FRUIT JUICE 1 mL/100 mL; VETIVERIA ZIZANOIDES ROOT OIL 1 mL/100 mL; ALMOND 15 mL/100 mL; BIOTIN 2 mL/100 mL; BEESWAX 30 mL/100 mL; AQUA 15 mL/100 mL; DAVANA OIL 5 g/100 mL; SILYBUM MARIANUM SEED OIL 2 mL/100 mL; SIMMONDSIA CHINENSIS (JOJOBA) SEED OIL 2 mL/100 mL; ROSEMARY OIL 5 mL/100 mL; BUTYROSPERMUM PARKII (SHEA) BUTTER 20 mL/100 mL

ACTIVE INGREDIENT

Batana Oil

minoxidil

PURPOSE

Hair growth, strengthens hair, repairs damaged hair

INSTRUCTIONS FOR USE

Apply directly to scalp and hair as pre-shampoo treatment; massage into scalp and leave in for 20-60 minutes before rinsing out with warm water and shampoo/conditioner routine

WARNINGS

Avoid contact with eyes or mouth

DOSAGE AND ADMINISTRATION

For external use only.

Stop use and ask a doctor if

chest pain, rapid heartbeat, faintness, or dizziness occurs

sudden, unexplained weight gain occurs

your hands or feet swell

scalp irritation or redness occurs

unwanted facial hair growth occurs

you do not see hair regrowth in 4 months

May be harmful if used when pregnant or breast-feeding.

Keep out of reach of children, lf swallowed, get medical help or contact a Poison Control Center right away.

WHEN USING

do not apply on other parts of the body

avoid contact with the eyes. in case of accidental contact, rinse eyes with large amounts of cool tap water

some people have experienced changes in hair color and/or texture

it takes time to regrow hair. Results may occur at 2 months with twice a day usage. For some people, you may need to use this product for at least 4 months before you see results.

the amount of hair regrowth is different for each person. This product will notwork for all men.

KEEP OUT OF REACH OF CHILDREN

If sxralowed, get medical help or contact a Poison Conirol Cenler ngiht away.

STOP USE

on broken or irritated scalp

INACTIVE INGREDIENT

BATANA
(ROSEMARY) OIL
BIOTIN
BUTYROSPERMUM PARKII (SHEA BUTTER)
BEESWAX
SWEET ALMOND OIL
(JOJOBA) SEED OIL
SILYBUM MARIANUM SEED OIL
PRUNUS AMYGDALUS DULCIS (SWEET ALMOND) OIL
OPUNTIA FICUS-INDICA FRUIT EXTRACT
VETIVERIA ZIZANOIDES ROOT OIL

INDICATIONS AND USAGE

Hair loss treatment and growing hair